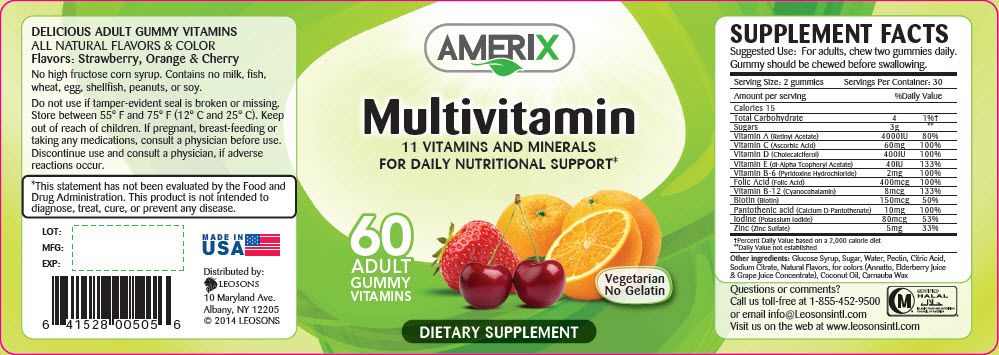 DRUG LABEL: Amerix Multivitamin
NDC: 69626-0505 | Form: TABLET, CHEWABLE
Manufacturer: Leosons Overseas Corporation
Category: other | Type: DIETARY SUPPLEMENT
Date: 20180912

ACTIVE INGREDIENTS: VITAMIN A ACETATE 2000 [iU]/1 1; ASCORBIC ACID 30 mg/1 1; CHOLECALCIFEROL 200 [iU]/1 1; .ALPHA.-TOCOPHEROL ACETATE 20 [iU]/1 1; PYRIDOXINE HYDROCHLORIDE 1 mg/1 1; FOLIC ACID 200 ug/1 1; CYANOCOBALAMIN 4 ug/1 1; BIOTIN 75 ug/1 1; CALCIUM PANTOTHENATE 5 mg/1 1; POTASSIUM IODIDE 40 ug/1 1; ZINC SULFATE, UNSPECIFIED FORM 2.5 mg/1 1; SUCROSE 1.5 g/1 1
INACTIVE INGREDIENTS: CORN SYRUP; WATER; PECTIN; CITRIC ACID MONOHYDRATE; ANNATTO; COCONUT OIL; CARNAUBA WAX

AMERIX Multivitamin

STATEMENT OF IDENTITY

SUPPLEMENT FACTS
Suggested Use: For adults, chew two gummies daily.
Gummy should be chewed before swallowing.
Serving Size: 2 gummies | Servings Per Container: 30
Amount per serving | %Daily Value
Calories 15
Total Carbohydrate | 4 | 1% [Percent Daily Value based on a 2,000 calorie diet]
Sugars | 3g | [Daily Value not established]
Vitamin A (Retinyl Acetate) | 4000IU | 80%
Vitamin C (Ascorbic Acid) | 60mg | 100%
Vitamin D (Cholecalciferol) | 400IU | 100%
Vitamin E (dl-Alpha Tcopheryl Acetate) | 40IU | 133%
Vitamin B-6 (Pyridoxine Hydrochloride) | 2mg | 100%
Folic Acid (Folic Acid) | 400mcg | 100%
Vitamin B-12 (Cyanocobalamin) | 8mcg | 133%
Biotin (Biotin) | 150mcg | 50%
Pantothenic acid (Calcium D-Pantothenate) | 10mg | 100%
Iodine (Potassium Iodide) | 80mcg | 53%
Zinc (Zinc Sulfate) | 5mg | 33%

Other ingredients: Glucose Syrup, Sugar, Water, Pectin, Citric Acid, Sodium Citrate, Natural Flavors, for colors (Annatto, Elderberry Juice & Grape Juice Concentrate), Coconut Oil, Carnauba Wax

HEALTH CLAIM

DELICIOUS ADULT GUMMY VITAMINS

ALL NATURAL FLAVORS & COLOR

Flavors: Strawberry, Orange & Cherry

No high fructose corn syrup. Contains no milk, fish, wheat, egg, shellfish, peanuts, or soy.

Do not use if tamper-evident seal is broken or missing. Store between 55° F and 75° F (12° C and 25° C). Keep out of reach of children. If pregnant, breast-feeding or taking any medications, consult a physician before use. Discontinue use and consult a physician, if adverse reactions occur.

HEALTH CLAIM

*This statement has not been evaluated by the Food and Drug Administration. This product is not intended to diagnose, treat, cure, or prevent any disease.

Questions or comments?

Call us toll-free at 1-855-452-9500 or email info@Leosonsintl.com

Visit us on the web at www.leosonsintl.com

HEALTH CLAIM

CERTIFIED
HALAL
ISLAMIC FOOD AND NUTRITION
COUNCIL OF AMERICA

HEALTH CLAIM

LOT:

MFG:

EXP:

MADE IN USA

Distributed by:
LEOSONS
10 Maryland Ave.
Albany, NY 12205
© 2014 LEOSONS

PRINCIPAL DISPLAY PANEL - 60 Vitamin Bottle Label

AMERIX

Multivitamin

11 VITAMINS AND MINERALS
FOR DAILY NUTRITIONAL SUPPORT*

60
ADULT
GUMMY
VITAMINS

Vegetarian
No Gelatin

DIETARY SUPPLEMENT